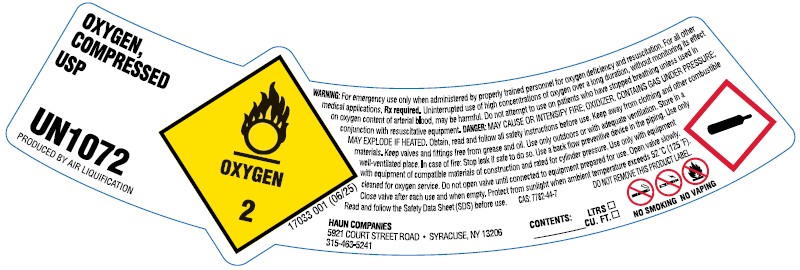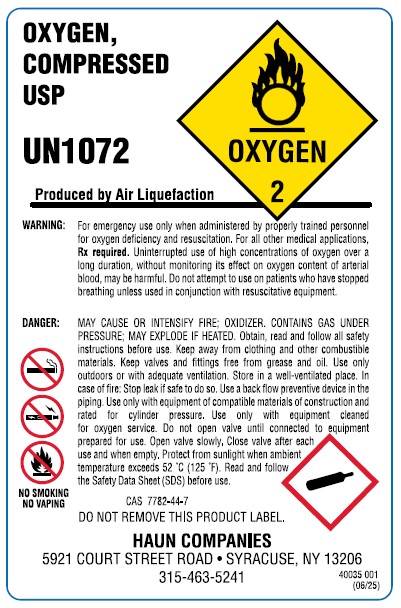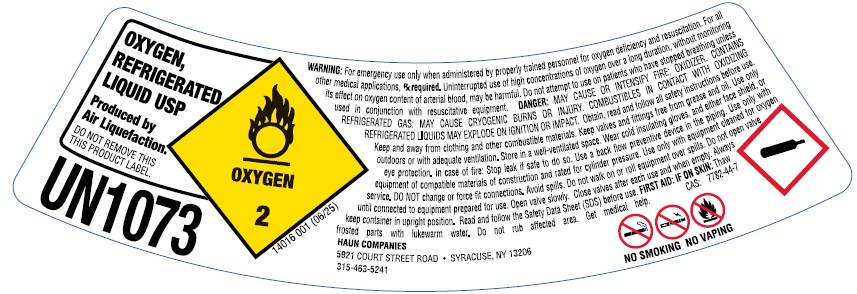 DRUG LABEL: Oxygen
NDC: 10526-005 | Form: GAS
Manufacturer: Haun Welding Supply, Inc.
Category: prescription | Type: HUMAN PRESCRIPTION DRUG LABEL
Date: 20251229

ACTIVE INGREDIENTS: OXYGEN 990 mL/1 L

Oxygen

PACKAGE LABEL

OXYGEN, COMPRESSED USP UN1072 PRODUCED BY AIR LIQUIFACTION OXYGEN 2
WARNING: For emergency use only when administered by properly trained personnel for oxygen deficiency and resuscitation. For all other medical applications, Rx only. Uninterrupted use of high concentrations of oxygen over a long duration, without monitoring its effect on oxygen content of arterial blood, may be harmful. Do not attempt to use on patients who have stopped breathing unless used in conjunction with resuscitative equipment. Keep out of reach of children. Federal law requires that this container be refilled with oxygen USP only by establishments registered as a drug manufacturer in accordance with the Federal Food, Drug and Cosmetic Act.
DANGER: MAY CAUSE OR INTENCIFY FIRE; OXYDIZER. CONTAINS GAS UNDER PRESSURE; MAY EXPLODE IF HEATED. Do not handle until all safety precautions have been read and understood. Keep and store away from clothing and other combustible materials. Keep valves and fittings free from grease and oil. Use and store only outdoors or in a well-ventilated place. In case of fire; Stop leak if safe to do so. Use a back flow preventive device in the piping. Use only with equipment of compatible materials of construction and rated for cylinder pressure. Use only with equipment cleaned for oxygen service. Open valve slowly. Close valve after each use and when empty. Protect from sunlight when ambient temperature exceeds 52 C (125 F). Read and follow the Safety Data Sheet (SDS) before use.
CAS: 7782-44-7 DO NOT REMOVE THIS PRODUCT LABEL
CONTENTS: LTRS CU. FT.
HAUN COMPANIES 5921 COURT STREET ROAD . SYRACUSE, NY 13206 315-463-5241

PACKAGE LABEL

OXYGEN, COMPRESSED USP UN1072 PRODUCED BY AIR LIQUIFACTION OXYGEN 2
WARNING: For emergency use only when administered by properly trained personnel for oxygen deficiency and resuscitation. For all other medical applications, Rx only. Uninterrupted use of high concentrations of oxygen over a long duration, without monitoring its effect on oxygen content of arterial blood, may be harmful. Do not attempt to use on patients who have stopped breathing unless used in conjunction with resuscitative equipment. Keep out of reach of children. Federal law requires that this container be refilled with oxygen USP only by establishments registered as a drug manufacturer in accordance with the Federal Food, Drug and Cosmetic Act.
DANGER: MAY CAUSE OR INTENCIFY FIRE; OXYDIZER. CONTAINS GAS UNDER PRESSURE; MAY EXPLODE IF HEATED. Do not handle until all safety precautions have been read and understood. Keep and store away from clothing and other combustible materials. Keep valves and fittings free from grease and oil. Use and store only outdoors or in a well-ventilated place. In case of fire; Stop leak if safe to do so. Use a back flow preventive device in the piping. Use only with equipment of compatible materials of construction and rated for cylinder pressure. Use only with equipment cleaned for oxygen service. Open valve slowly. Close valve after each use and when empty. Protect from sunlight when ambient temperature exceeds 52 C (125 F). Read and follow the Safety Data Sheet (SDS) before use.
CAS: 7782-44-7 DO NOT REMOVE THIS PRODUCT LABEL
HAUN COMPANIES 5921 COURT STREET ROAD . SYRACUSE, NY 13206 315-463-5241

PACKAGE LABEL

OXYGEN, REFRIGERATED LIQUID USP UN1073 OXYGEN 2 Produced by Air Liquefaction. DO NOT REMOVE THIS PRODUCT LABEL.
WARNING: For emergency use only when administered by properly trained personnel for oxygen deficiency and resuscitation. For all other medical applications, Rx only. Uninterrupted use of high concentrations of oxygen over a long duration, without monitoring its effect on oxygen content of arterial blood, may be harmful. Do not attempt to use on patients who have stopped breathing unless used in conjunction with resuscitative equipment. Keep out of reach of children. Federal law requires that this container be filled with oxygen USP only by establishments registered as a drug manufacturer in accordance with the Federal Food, Drug, and Cosmetic Act.
DANGER: MAY CAUSE OR INTENSIFY FIRE; OXYDIZER. CONTAINS REFRIGERATED GAS; MAY CAUSE CRYOGENIC BURNS OR INJURY. COMBUSTIBLES IN CONTACT WITH LIQUID OXYGEN MAY EXPLODE ON IGNITION OR IMPACT. Do not handle until all safety precautions have been read and understood. Keep and store away from clothing and other combustible materials. Keep valves and fittings free from grease and oil. Use and store only outdoors or in a well-ventilated place. Wear cold insulating gloves, face shield, and eye protection. In case of fire; Stop leak if safe to do so. Use a back flow preventive device in the piping. Use only with equipment of compatible materials of construction and rated for cylinder pressure. Use only with equipment cleaned for oxygen service. DO NOT change or force fit connections. Avoid spills, Do not walk on or roll equipment over spills. Close valve after each use and when empty. Always keep container in upright position. Read and follow the Safety Data Sheet (SDS) before use.
FIRST AID: IF ON SKIN: Thaw frosted parts with lukewarm water. Do not rub affected area. Get immediate medical advice/attention. CAS: 7782-44-7
HAUN COMPANIES 5921 COURT STREET ROAD . SYRACUSE, NY 13206 315-463-5241